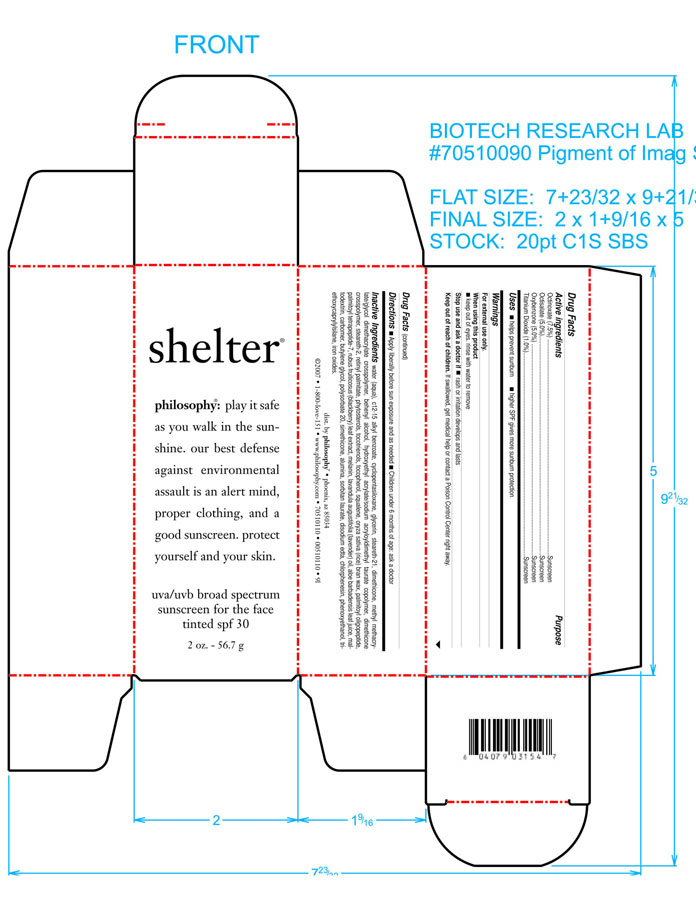 DRUG LABEL: Shelter Tinted
NDC: 50184-4700 | Form: CREAM
Manufacturer: Philosophy, Inc.
Category: otc | Type: HUMAN OTC DRUG LABEL
Date: 20100211

ACTIVE INGREDIENTS: octinoxate 75 mg/1 g; OCTISALATE 50 mg/1 g; OXYBENZONE 50 mg/1 g; TITANIUM DIOXIDE 10 mg/1 g
INACTIVE INGREDIENTS: WATER; C12-15 ALKYL BENZOATE; CYCLOMETHICONE 5; GLYCERIN; STEARETH-21; DIMETHICONE; METHYL METHACRYLATE; DOCOSANOL; STEARETH-2; VITAMIN A PALMITATE; ALPHA-TOCOPHEROL; SQUALENE; RICE BRAN; RUBUS FRUTICOSUS LEAF ; ENGLISH LAVENDER OIL; ALOE VERA LEAF  ; MALTODEXTRIN; CARBOMER 934; BUTYLENE GLYCOL; POLYSORBATE 20; ALUMINUM OXIDE; SORBITAN MONOLAURATE; EDETATE DISODIUM; CHLORPHENESIN; PHENOXYETHANOL; OCTYLTRIETHOXYSILANE ; FERRIC OXIDE YELLOW; FERRIC OXIDE RED

DRUG FACTS

INACTIVE INGREDIENT

WATER (AQUA)

C12-15 ALKYL BENZOATE

CYCLOPENTASILOXANE

GLYCERIN

STEARETH-21

DIMETHICONE

METHYL METHACRYLATE/GLYCOL DIMETHACRYLATE CROSSPOLYMER

BEHENYL ALCOHOL

HYDROXYETHYL ACRYLATE/SODIUM ACRYLOYLDIMETHYL TAURATE COPOLYMER

DIMETHICONE CROSSPOLYMER

STEARETH-2

RETINYL PALMITATE

PHYTOSTEROLS

TOCOTRIENOLS

TOCOPHEROL

SQUALENE

ORYZA SATIVA (RICE) BRAN WAX

PALMITOYL OLIGOPEPTIDE

PALMITOYL TETRAPEPTIDE-7

RUBUS FRUITICOSUS (BLACKBERRY) LEAF EXTRACT

MELANIN

LAVANDULA AUGUSTIFOLIA (LAVENDER) OIL

ALOE BARBADENSIS LEAF JUICE

MALTODEXTRIN

CARBOMER

BUTYLENE GLYCOL

POLYSORBATE 20

SIMETHICONE

ALUMINA

SORBITAN LAURATE

DISODIUM EDTA

CHLORPHENESIN

PHENOXYETHANOL

TRIETHOXYCAPRYLYLSILANE

IRON OXIDES

ASK DOCTOR IF RASH OR IRRITATION DEVELOPS AND LASTS

WHEN USING THIS PRODUCT. KEEP OUT OF EYES, RINSE WITH WATER TO REMOVE.

STOP USE AND ASK A DOCTOR IS RASH OCCURS AND LASTS.

KEEP OUT OF REACH OF CHILDREN, IF SWALLOWED GET MEDICAL HELP OR CONTACT A POISON CENTER RIGHT AWAY

PACKAGE LABEL

Enter section text here